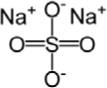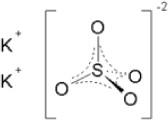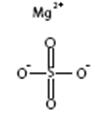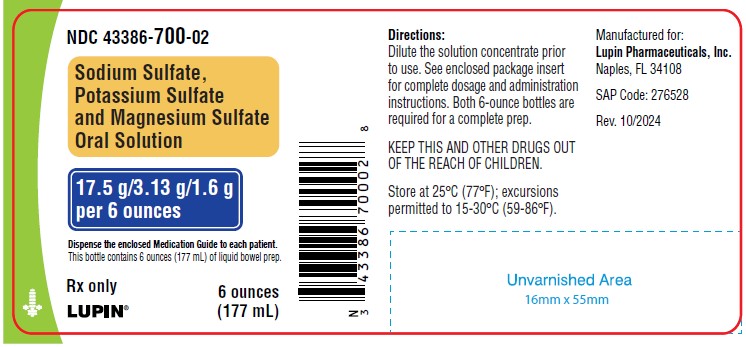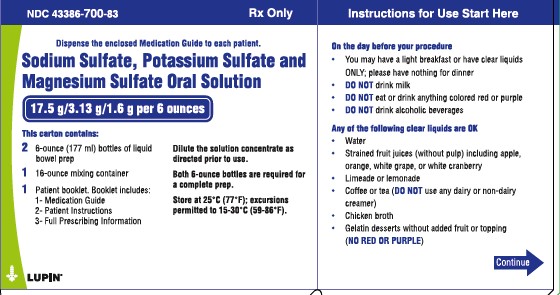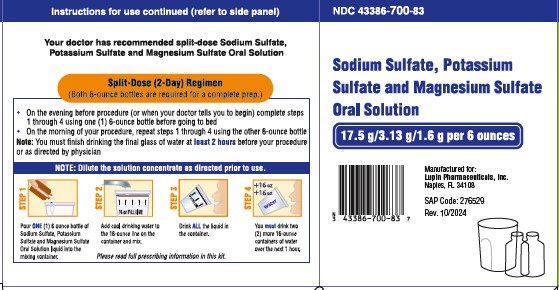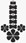 DRUG LABEL: SODIUM SULFATE, POTASSIUM SULFATE, MAGNESIUM SULFATE
NDC: 43386-700 | Form: SOLUTION
Manufacturer: Lupin Pharmaceuticals, Inc.
Category: prescription | Type: HUMAN PRESCRIPTION DRUG LABEL
Date: 20251215

ACTIVE INGREDIENTS: SODIUM SULFATE 17.5 g/177 mL; POTASSIUM SULFATE 3.13 g/177 mL; MAGNESIUM SULFATE ANHYDROUS 1.6 g/177 mL
INACTIVE INGREDIENTS: MALIC ACID; ANHYDROUS CITRIC ACID; SODIUM BENZOATE; WATER; SUCRALOSE

HIGHLIGHTS OF PRESCRIBING INFORMATION

These highlights do not include all the information needed to use SODIUM SULFATE, POTASSIUM SULFATE, MAGNESIUM SULFATE safely and effectively. See full prescribing information for SODIUM SULFATE, POTASSIUM SULFATE, MAGNESIUM SULFATE.
SODIUM SULFATE, POTASSIUM SULFATE, MAGNESIUM SULFATE (sodium sulfate, potassium sulfate, magnesium sulfate) SOLUTION for ORAL use.
Initial U.S. Approval: 2010

1 INDICATIONS & USAGE

Sodium Sulfate, Potassium Sulfate and Magnesium Sulfate Oral Solution is an osmotic laxative indicated for cleansing of the colon in preparation for colonoscopy in adults (1)

2 DOSAGE & ADMINISTRATION

Dilute the solution prior to use. See FULL PRESCRIBING INFORMATION for complete dosing and administration instructions (2)

Split Dose (2-Day) Regimen

- Evening before colonoscopy: dilute one bottle with water to a total volume of 16 ounces (up to the fill line) and drink the entire amount.
- Drink 32 ounces of water over the next hour.
- Next morning: repeat both steps using the second bottle.
- Complete preparation at least 2 hours before colonoscopy or as directed by physician.

3 DOSAGE FORMS & STRENGTHS

- Two 6 ounce bottles of oral solution, each containing sodium sulfate 17.5 grams, potassium sulfate 3.13 grams, and magnesium sulfate 1.6 grams. (3)

4 CONTRAINDICATIONS

- Gastrointestinal obstruction (4, 5.6)
- Bowel perforation (4, 5.6)
- Gastric retention (4)
- Ileus (4)
- Toxic colitis or toxic megacolon (4)
- Known allergies to components of the kit (4, 11)

5 WARNINGS AND PRECAUTIONS

- Risk of fluid and electrolyte abnormalities, arrhythmias, seizures and renal impairment– assess concurrent medications and consider testing in some patients (5.1, 5.2, 5.3)
- Patients with renal insufficiency– use caution, ensure adequate hydration and consider testing (5.4)
- Suspected GI obstruction or perforation – rule out the diagnosis before administration (4, 5.6)
- Patients at risk for aspiration – observe during administration (5.7)
- Not for direct ingestion – dilute and take with additional water (5.8)

6 ADVERSE REACTIONS

Most common adverse reactions (≥3%) are: overall discomfort, abdominal fullness, nausea, abdominal cramping, and vomiting (6)

To report SUSPECTED ADVERSE REACTIONS, contact Lupin Pharmaceuticals, Inc. at 1-866-403-7592 or FDA at 1-800-FDA-1088 or www.fda.gov/medwatch.

7 DRUG INTERACTIONS

- Some drugs increase risks due to fluid and electrolyte changes (7.1)
- Oral medication taken within 1 hour of start of each dose might not be absorbed properly (7.2)

RECENT MAJOR CHANGES

Dosage and Administration 11/2012

FULL PRESCRIBING INFORMATION

1 INDICATIONS & USAGE

Sodium Sulfate, Potassium Sulfate and Magnesium Sulfate Oral Solution is indicated for cleansing of the colon as a preparation for colonoscopy in adults.

2 DOSAGE & ADMINISTRATION

Sodium Sulfate, Potassium Sulfate and Magnesium Sulfate Oral Solution should be taken as a split-dose oral regimen.

The dose for colon cleansing requires administration of two bottles of Sodium Sulfate, Potassium Sulfate and Magnesium Sulfate Oral Solution. Each bottle is administered as 16 ounces of diluted Sodium Sulfate, Potassium Sulfate and Magnesium Sulfate Oral Solution with an additional 1 quart of water taken orally. The total volume of liquid required for colon cleansing (using two bottles) is 3 quarts (approximately 2.8 L) taken orally prior to the colonoscopy in the following way:

Split-Dose (Two-Day) Regimen

Day prior to colonoscopy:

- A light breakfast may be consumed, or have only clear liquids on the day before colonoscopy. Avoid red and purple liquids, milk, and alcoholic beverages.
- Early in the evening prior to colonoscopy: pour the contents of one bottle of Sodium Sulfate, Potassium Sulfate and Magnesium Sulfate Oral Solution into the mixing container provided. Fill the container with water to the 16 ounce fill line, and drink the entire amount.
- Drink two additional containers filled to the 16 ounce line with water over the next hour.

Day of colonoscopy:

- Have only clear liquids until after the colonoscopy. Avoid red and purple liquids, milk, and alcoholic beverages.
- The morning of colonoscopy (10 to 12 hours after the evening dose): pour the contents of the second bottle of Sodium Sulfate, Potassium Sulfate and Magnesium Sulfate Oral Solution into the mixing container provided. Fill the container with water to the 16 ounce fill line, and drink the entire amount.
- Drink two additional containers filled to the 16 ounce line with water over the next hour.
- Complete all Sodium Sulfate, Potassium Sulfate and Magnesium Sulfate Oral Solution and required water at least two hours prior to colonoscopy or as directed by physician.

3 DOSAGE FORMS & STRENGTHS

- Two 6 ounce bottles of oral solution.
  Each 6 ounce bottle contains: sodium sulfate 17.5 grams, potassium sulfate 3.13 grams, magnesium sulfate 1.6 grams.

4 CONTRAINDICATIONS

- Gastrointestinal obstruction
- Bowel perforation
- Gastric retention
- Ileus
- Toxic colitis or toxic megacolon
- Known allergies to components of the kit [see Description (11)]

5 WARNINGS AND PRECAUTIONS

5.1 Serious Fluid and Serum Chemistry Abnormalities

Advise all patients to hydrate adequately before, during, and after the use of Sodium Sulfate, Potassium Sulfate and Magnesium Sulfate Oral Solution. If a patient develops significant vomiting or signs of dehydration after taking Sodium Sulfate, Potassium Sulfate and Magnesium Sulfate Oral Solution, consider performing post-colonoscopy lab tests (electrolytes, creatinine, and BUN). Fluid and electrolyte disturbances can lead to serious adverse events including cardiac arrhythmias, seizures and renal impairment.

Patients with electrolyte abnormalities should have them corrected before treatment with Sodium Sulfate, Potassium Sulfate and Magnesium Sulfate Oral Solution. In addition, use caution when prescribing Sodium Sulfate, Potassium Sulfate and Magnesium Sulfate Oral Solution for patients with conditions, or who are using medications, that increase the risk for fluid and electrolyte disturbances or may increase the risk of adverse events of seizure, arrhythmias, and renal impairment. [See Drug Interactions (7.1)]

Sodium Sulfate, Potassium Sulfate and Magnesium Sulfate Oral Solution can cause temporary elevations in uric acid. [See Adverse Reactions (6.1)]. Uric acid fluctuations in patients with gout may precipitate an acute flare. The potential for uric acid elevation should be considered before administering Sodium Sulfate, Potassium Sulfate and Magnesium Sulfate Oral Solution to patients with gout or other disorders of uric acid metabolism.

5.2 Cardiac Arrhythmias

There have been rare reports of serious arrhythmias associated with the use of ionic osmotic laxative products for bowel preparation. Use caution when prescribing Sodium Sulfate, Potassium Sulfate and Magnesium Sulfate Oral Solution for patients at increased risk of arrhythmias (e.g., patients with a history of prolonged QT, uncontrolled arrhythmias, recent myocardial infarction, unstable angina, congestive heart failure, or cardiomyopathy). Pre-dose and post-colonoscopy ECGs should be considered in patients at increased risk of serious cardiac arrhythmias.

5.3 Seizures

There have been reports of generalized tonic-clonic seizures and/or loss of consciousness associated with use of bowel preparation products in patients with no prior history of seizures. The seizure cases were associated with electrolyte abnormalities (e.g., hyponatremia, hypokalemia, hypocalcemia, and hypomagnesemia) and low serum osmolality. The neurologic abnormalities resolved with correction of fluid and electrolyte abnormalities.

Use caution when prescribing Sodium Sulfate, Potassium Sulfate and Magnesium Sulfate Oral Solution for patients with a history of seizures and in patients at increased risk of seizure, such as patients taking medications that lower the seizure threshold (e.g., tricyclic antidepressants), patients withdrawing from alcohol or benzodiazepines, or patients with known or suspected hyponatremia.

5.4 Renal Impairment

Use caution when prescribing Sodium Sulfate, Potassium Sulfate and Magnesium Sulfate Oral Solution for patients with impaired renal function or patients taking concomitant medications that may affect renal function (such as diuretics, angiotensin converting enzyme inhibitors, angiotensin receptor blockers, or non-steroidal anti-inflammatory drugs). Advise these patients of the importance of adequate hydration, and consider performing baseline and post-colonoscopy laboratory tests (electrolytes, creatinine, and BUN) in these patients.

5.5 Colonic Mucosal Ulcerations and Ischemic Colitis

Administration of osmotic laxative products may produce colonic mucosal aphthous ulcerations, and there have been reports of more serious cases of ischemic colitis requiring hospitalization. Concurrent use of stimulant laxatives and Sodium Sulfate, Potassium Sulfate and Magnesium Sulfate Oral Solution may increase these risks. The potential for mucosal ulcerations resulting from the bowel preparation should be considered when interpreting colonoscopy findings in patients with known or suspect inflammatory bowel disease (IBD).

5.6 Use in Patients with Significant Gastrointestinal Disease

If gastrointestinal obstruction or perforation is suspected, perform appropriate diagnostic studies to rule out these conditions before administering Sodium Sulfate, Potassium Sulfate and Magnesium Sulfate Oral Solution.

Use with caution in patients with severe active ulcerative colitis.

5.7 Aspiration

Use with caution in patients with impaired gag reflex and patients prone to regurgitation or aspiration. Such patients should be observed during administration of Sodium Sulfate, Potassium Sulfate and Magnesium Sulfate Oral Solution.

5.8 Not for Direct Ingestion

Each bottle must be diluted with water to a final volume of 16 ounces and ingestion of additional water as recommended is important to patient tolerance. Direct ingestion of the undiluted solution may increase the risk of nausea, vomiting, dehydration, and electrolyte disturbances.

6 ADVERSE REACTIONS

6.1 Clinical Studies Experience

Because clinical studies are conducted under widely varying conditions, adverse reaction rates observed in the clinical studies of a drug cannot be directly compared to rates in clinical studies of another drug and may not reflect the rates observed in practice.

In a multicenter, controlled clinical trial comparing Sodium Sulfate, Potassium Sulfate and Magnesium Sulfate Oral Solution with a bowel prep containing polyethylene glycol and electrolytes (PEG + E) that were administered in a split-dose (2-day) regimen, the most common adverse reactions after administration of Sodium Sulfate, Potassium Sulfate and Magnesium Sulfate Oral Solution were overall discomfort, abdominal distention, abdominal pain, nausea, vomiting, and headache; see Table 1, below. Less common Adverse Reactions occurring were AV Block (1 case) and CK increase. In this study, patients receiving Sodium Sulfate, Potassium Sulfate and Magnesium

Sulfate Oral Solution were limited to a light breakfast followed by clear liquids; patients receiving the PEG + E bowel prep were allowed to have a normal breakfast and a light lunch, followed by clear liquids.

Table 1: Treatment-Emergent Adverse Reactions Observed in at Least 2% of Patients on the Split-Dose (2-Day) Regimen
Symptom | Split-Dose (2-Day) Regimen
Symptom | Sodium Sulfate, Potassium Sulfate and MagnesiumSulfate Oral SolutionN=190 | PEG + EProductN=189
Overall Discomfort | 54% | 67%
Abdominal Distension | 40% | 52%
Abdominal Pain | 36% | 43%
Nausea | 36% | 33%
Vomiting | 8% | 4%
Headache | 1.1% | 0.5%

Table 2 shows the percentages of patients who developed new abnormalities of important electrolytes and uric acid after completing the bowel preparation with either Sodium Sulfate, Potassium Sulfate and Magnesium Sulfate Oral Solution or PEG+E administered as a split-dose (2-day) regimen.

Table 2: Patients with Normal Baseline Serum Chemistry with A Shift to an Abnormal Value While on the Split-Dose (2-Day) Regimen
 |  | Day of Colonoscopy n (%)* | Day 30 n (%)*
Anion gap (high) † | Sodium Sulfate, Potassium Sulfate and Magnesium Sulfate Oral Solution | 14 (8.9) | 3 (1.9)
 | PEG + Electrolytes | 12 (7.6) | 2 (1.4)
Bicarbonate (low) | Sodium Sulfate, Potassium Sulfate and Magnesium Sulfate Oral Solution | 20 (12.7) | 7 (4.4)
 | PEG + Electrolytes | 24 (15.2) | 4 (2.7)
Bilirubin, total (high) | Sodium Sulfate, Potassium Sulfate and Magnesium Sulfate Oral Solution | 14 (8.5) | 0 (0)
 | PEG + Electrolytes | 20 (11.7) | 3 (1.9)
BUN (high) | Sodium Sulfate, Potassium Sulfate and Magnesium Sulfate Oral Solution | 2 (1.6) | 14 (11.2)
 | PEG + Electrolytes | 4 (2.9) | 19 (14.5)
Calcium (high) | Sodium Sulfate, Potassium Sulfate and Magnesium Sulfate Oral Solution | 16 (10.4) | 8 (5.2)
 | PEG + Electrolytes | 6 (3.7) | 6 (3.9)
Chloride (high) | Sodium Sulfate, Potassium Sulfate and Magnesium Sulfate Oral Solution | 4 (2.4) | 6 (3.7)
 | PEG + Electrolytes | 20 (12.2) | 6 (3.8)
Creatinine (high) | Sodium Sulfate, Potassium Sulfate and Magnesium Sulfate Oral Solution | 3 (1.9) | 5 (3.2)
 | PEG + Electrolytes | 2 (1.2) | 8 (5.2)
Osmolality (high) | Sodium Sulfate, Potassium Sulfate and Magnesium Sulfate Oral Solution | 8 (5.8) | NA
 | PEG + Electrolytes | 19 (12.9) | NA
Osmolality (low) | Sodium Sulfate, Potassium Sulfate and Magnesium Sulfate Oral Solution | 3 (2.2) | NA
 | PEG + Electrolytes | 2 (1.4) | NA
Potassium (high) | Sodium Sulfate, Potassium Sulfate and Magnesium Sulfate Oral Solution | 3 (1.8) | 6 (3.7)
 | PEG + Electrolytes | 5 (2.9) | 8 (4.9)
Sodium (low) | Sodium Sulfate, Potassium Sulfate and Magnesium Sulfate Oral Solution | 5 (3.1) | 1 (0.6)
 | PEG + Electrolytes | 4 (2.3) | 2 (1.2)
Uric acid (high) | Sodium Sulfate, Potassium Sulfate and Magnesium Sulfate Oral Solution | 27 (23.5) | 13 (11.5)
 | PEG + Electrolytes | 12 (9.5) | 20 (16.7)

*Percent (n/N) of patients where N=number of patients with normal baseline who had abnormal values at the timepoint(s) of interest.

†Patients with normal bicarbonate at baseline who developed low bicarbonate (≤ 21 mEq/L) and high anion gap (≥ 13 mEq/L) on Day of Colonoscopy or Day 30.

There were also 408 patients who participated in a study in which either Sodium Sulfate, Potassium Sulfate and Magnesium Sulfate Oral Solution or PEG+E were administered in an evening-only (1-day) regimen. Higher rates of overall discomfort, abdominal distention, and nausea were observed with the evening-only (1-day) regimen compared to the split-dose (2-day) regimen for both preparations. Patients treated with Sodium Sulfate, Potassium Sulfate and Magnesium Sulfate Oral Solution had increased rates of vomiting with the evening-only (1-day) regimen. An evening-only (1-day) dosing

regimen was associated with higher rates of abnormal values for some electrolytes when compared to the split-dose (2-day) regimen for both preparations. For Sodium Sulfate, Potassium Sulfate and Magnesium Sulfate Oral Solution, the evening-only (1-day) regimen was associated with higher rates of total bilirubin (high), BUN (high), creatinine (high), osmolality (high), potassium (high) and uric acid (high) than the Sodium Sulfate, Potassium Sulfate and Magnesium Sulfate Oral Solution split dose (2-day) regimen. Administration of Sodium Sulfate, Potassium Sulfate and Magnesium Sulfate Oral Solution in an evening-only (1-day) dosing regimen is not recommended.

7 DRUG INTERACTIONS

7.1 Drugs That May Increase Risks Due to Fluid and Electrolyte Abnormalities

Use caution when prescribing Sodium Sulfate, Potassium Sulfate and Magnesium Sulfate Oral Solution for patients with conditions, or who are using medications, that increase the risk for fluid and electrolyte disturbances or may increase the risk of adverse events of seizure, arrhythmias, and prolonged QT in the setting of fluid and electrolyte abnormalities. Consider additional patient evaluations as appropriate [see Warnings (5)] in patients taking these concomitant medications.

7.2 Potential for Altered Drug Absorption

Oral medication administered within one hour of the start of each Sodium Sulfate, Potassium Sulfate and Magnesium Sulfate Oral Solution dose may be flushed from the gastrointestinal tract, and the medication may not be absorbed properly.

8 USE IN SPECIFIC POPULATIONS

8.1 Pregnancy

Teratogenic effects: Pregnancy Category C. Animal reproduction studies have not been conducted with Sodium Sulfate, Potassium Sulfate and Magnesium Sulfate Oral Solution. It is also not known whether Sodium Sulfate, Potassium Sulfate and Magnesium Sulfate Oral Solution can cause fetal harm when administered to a pregnant woman or can affect reproduction capacity. Sodium Sulfate, Potassium Sulfate and Magnesium Sulfate Oral Solution should be given to a pregnant woman only if clearly needed.

8.3 Nursing Mothers

It is not known whether this drug is excreted in human milk. Because many drugs are excreted in human milk, caution should be exercised when Sodium Sulfate, Potassium Sulfate and Magnesium Sulfate Oral Solution is administered to a nursing woman.

8.4 Pediatric Use

Safety and effectiveness in pediatric patients have not been established.

8.5 Geriatric Use

Of the 375 patients who received Sodium Sulfate, Potassium Sulfate and Magnesium Sulfate Oral Solution in clinical trials, 94 (25%) were 65 years of age or older, and 25 (7%) were 75 years of age or older. No overall differences in safety or effectiveness of Sodium Sulfate, Potassium Sulfate and Magnesium Sulfate Oral Solution administered as a split-dose (2-day) regimen were observed between geriatric patients and younger patients. Geriatric patients reported more vomiting when Sodium Sulfate, Potassium Sulfate and Magnesium Sulfate Oral Solution was given as a one-day preparation.

11 DESCRIPTION

Each Sodium Sulfate, Potassium Sulfate and Magnesium Sulfate Oral Solution contains two 6 ounce bottles of solution. Each 6 ounce bottle contains: sodium sulfate 17.5 grams, potassium sulfate 3.13 grams, magnesium sulfate 1.6 grams. Inactive ingredients include: sodium benzoate, sucralose, malic acid, citric acid, lemon flavor, purified water. The solution is a clear to slightly hazy liquid. The solution is clear and colorless when diluted to a final volume of 16 ounces with water.

Sodium Sulfate, USP

The chemical name is Na2SO4.

The average Molecular Weight is 142.04. The structural formula is:

Potassium Sulfate, FCC, Granular

The chemical name is K2 SO4.

The average Molecular Weight is 174.26. The structural formula is:

Magnesium Sulfate, USP

The chemical name is MgSO4.

The average Molecular Weight: 120.37. The structural formula is:

Each Sodium Sulfate, Potassium Sulfate and Magnesium Sulfate Oral Solution package also contains a polypropylene mixing container.

12 CLINICAL PHARMACOLOGY

12.1 Mechanism of Action

Sulfate salts provide sulfate anions, which are poorly absorbed. The osmotic effect of unabsorbed sulfate anions and the associated cations causes water to be retained within the gastrointestinal tract.

12.2 Pharmacodynamics

The osmotic effect of the unabsorbed ions, when ingested with a large volume of water, produces a copious watery diarrhea.

12.3 Pharmacokinetics

Fecal excretion was the primary route of sulfate elimination. After administration of Sodium Sulfate, Potassium Sulfate and Magnesium Sulfate Oral Solution in six healthy volunteers, the time at which serum sulfate reached its highest point (Tmax) was approximately 17 hours after the first half dose or approximately 5 hours after the second dose, and then declined with a half-life of 8.5 hours.

The disposition of sulfate after Sodium Sulfate, Potassium Sulfate and Magnesium Sulfate Oral Solution was also studied in patients (N=6) with mild-moderate hepatic impairment (Child-Pugh grades A and B) and in patients (N=6) with moderate renal impairment (creatinine clearance of 30 to 49 mL/min). The renal impairment group had the highest serum sulfate AUC and Cmax, followed by the hepatic impairment group, and then by healthy subjects. Systemic exposure of serum sulfate (AUC and Cmax) was similar between healthy subjects and hepatic impairment patients. Renal impairment resulted in 54% higher mean AUC and 44% higher mean Cmax than healthy subjects. The mean sulfate levels of all three groups returned to their respective baseline levels by Day 6 after dose initiation. Urinary excretion of sulfate over 30 hours, starting after the first half dose, was similar between hepatic patients and normal volunteers, but was approximately 16% lower in moderate renal impairment patients than in healthy volunteers.

13 NONCLINICAL TOXICOLOGY

13.1 Carcinogenesis, Mutagenesis, Impairment of Fertility

Long-term studies in animals have not been performed to evaluate the carcinogenic potential of Sodium Sulfate, Potassium Sulfate and Magnesium Sulfate Oral Solution. Studies to evaluate the possible impairment of fertility or mutagenic potential of Sodium Sulfate, Potassium Sulfate and Magnesium Sulfate Oral Solution have not been performed.

13.2 Animal Toxicology and/or Pharmacology

The sulfate salts of sodium, potassium, and magnesium contained in Sodium Sulfate, Potassium Sulfate and Magnesium Sulfate Oral Solution were administered orally (gavage) to rats and dogs up to 28 days up to a maximum daily dose of 5 grams/kg/day (approximately 0.9 and 3 times for rats and dogs, respectively, the recommended human dose of 44 grams/day or 0.89 grams/kg based on the body surface area). In rats, the sulfate salts caused diarrhea and electrolyte and metabolic changes, including hypochloremia, hypokalemia, hyponatremia, lower serum osmolality, and high serum bicarbonate. Significant renal changes included increased fractional sodium excretion, increased urinary sodium and potassium excretion, and alkaline urine in both males and females. In addition, creatinine clearance was significantly decreased in females at the highest dose. No microscopic renal changes were seen. In dogs, the sulfate salts caused emesis, excessive salivation, excessive drinking of water, and abnormal excreta (soft and/or mucoid feces and/or diarrhea) and increased urine pH and sodium excretion.

14 CLINICAL STUDIES

The colon cleansing efficacy of Sodium Sulfate, Potassium Sulfate and Magnesium Sulfate Oral Solution was evaluated in a randomized, single-blind, active-controlled, multicenter study. In this study, 363 adult patients were included in the efficacy analysis. Patients ranged in age from 20 to 84 years (mean age 55 years) and 54% were female. Race distribution was 86% Caucasian, 9% African-American, and 5% other.

Patients were randomized to one of the following two colon preparation regimens: Sodium Sulfate, Potassium Sulfate and Magnesium Sulfate Oral Solution or a marketed polyethylene glycol (PEG) bowel prep. In the Study Sodium Sulfate, Potassium Sulfate and Magnesium Sulfate Oral Solution was administered according to a split-dose preparation regimen [see Dosage and Administration (2)]. The PEG bowel prep was also given as a split-dose preparation according to its labeled instructions. Patients receiving Sodium Sulfate, Potassium Sulfate and Magnesium Sulfate Oral Solution were limited to a light breakfast followed by clear liquids on the day prior to the day of colonoscopy; patients receiving the PEG bowel prep were allowed to have a normal breakfast and a light lunch, followed by clear liquids.

The primary efficacy endpoint was the proportion of patients with successful colon cleansing as assessed by the colonoscopists, who were not informed about the type of preparation received. In the study, no clinically or statistically significant differences were seen between the group treated with Sodium Sulfate, Potassium Sulfate and Magnesium Sulfate Oral Solution and the group treated with the PEG bowel prep. See Table 3 below.

Table 3: Colon Cleansing Response Rates
Treatment Group | Regimen | N | Responders^1%(95% C. I.) | Sodium Sulfate, Potassium Sulfate and Magnesium Sulfate Oral Solution – PEG Difference (95% CI)
Sodium Sulfate, Potassium Sulfate and Magnesium Sulfate Oral Solution (With light breakfast) | Split-Dose | 180 | 97% (94%, 99%) | 2%^2 (-2%, 5%)
PEG bowel prep (with normal breakfast & light lunch) | Split-Dose | 183 | 96% (92%, 98%) | 2%^2 (-2%, 5%)
^1 Responders were patients whose colon preparations were graded excellent (no more than small bits of adherent feces/fluid) or good (small amounts of feces or fluid not interfering with the exam) by the colonoscopist.
^2 Does not equal difference in tabled responder rates due to rounding effects.

16 HOW SUPPLIED/STORAGE AND HANDLING

Each Sodium Sulfate, Potassium Sulfate and Magnesium Sulfate Oral Solution contains:

• Two (2) 6 ounce bottles of oral solution.

• One (1) 19 ounce mixing container with a 16 ounce fill line.

Storage:

Store at 20º to 25°C (68º to 77°F). Excursions permitted between 15º to 30°C (59º to 86°F). See USP controlled room temperature.

Keep out of reach of children.

Sodium Sulfate, Potassium Sulfate and Magnesium Sulfate Oral Solution Package NDC 43386-700-83

17 PATIENT COUNSELING INFORMATION

See Medication Guide and FDA -Approved Patient Labeling

17.1 Patient Counseling

• Ask patients to let you know if they have trouble swallowing or are prone to regurgitation or aspiration.

• Instruct patients that each bottle needs to be diluted in water before ingestion and that they need to drink additional water according to the instructions. Direct ingestion of the undiluted solution may increase the risk of nausea, vomiting, and dehydration.

• Inform patients that oral medications may not be absorbed properly if they are taken within one hour of starting each dose of Sodium Sulfate, Potassium Sulfate and Magnesium Sulfate Oral Solution.

• Tell patients not to take other laxatives while they are taking Sodium Sulfate, Potassium Sulfate and Magnesium Sulfate Oral Solution.

LUPIN and the are registered trademarks of Lupin Pharmaceuticals, Inc.

Lupin Pharmaceuticals, Inc.

Naple, FL 34018

SAP Code: 276530

Revised 10/2024

RECENT MAJOR CHANGES

Manufactured for:

Lupin Pharmaceuticals, Inc.

Baltimore, MD 21202

SAP Code: 269305

Revised 11/2021

Medication Guide

Sodium Sulfate (soe' dee um sul' fate), Potassium Sulfate (poe tas' ee um sul' fate) and Magnesium Sulfate (mag nee' zee um sul' fate) Oral Solution

Read this Medication Guide before you start taking Sodium Sulfate, Potassium Sulfate and Magnesium Sulfate oral solution. This information does not take the place of talking with your healthcare provider about your medical condition or your treatment.

What is the most important information I should know about Sodium Sulfate, Potassium Sulfate and Magnesium Sulfate Oral Solution?

Sodium Sulfate, Potassium Sulfate and Magnesium Sulfate Oral Solution and other osmotic bowel preparations can cause serious side effects, including:

Serious loss of body fluid (dehydration) and changes in blood salts (electrolytes) in your blood.

These changes can cause:

• abnormal heartbeats that can cause death

• seizures. This can happen even if you have never had a seizure.

• kidney problems

Your chance of having fluid loss and changes in body salts with Sodium Sulfate,

Potassium Sulfate and Magnesium Sulfate Oral Solution is higher if you:

- have heart problems
- have kidney problems
- take water pills or non-steroidal anti-inflammatory drugs (NSAIDS)

Tell your healthcare provider right away if you have any of these symptoms of a loss of too much body fluid (dehydration) while taking Sodium Sulfate,

Potassium Sulfate and Magnesium Sulfate Oral Solution:

- vomiting that prevents you from keeping down the additional prescribed amount of water listed in the Instructions for Use in the Patient Instructions for Use Booklet
- dizziness
- urinating less often than normal
- headache

See Section “What are the possible side effects of Sodium Sulfate, Potassium

Sulfate and Magnesium Sulfate Oral Solution?” for more information about side effects.

What is Sodium Sulfate, Potassium Sulfate and Magnesium Sulfate Oral

Solution?

Sodium Sulfate, Potassium Sulfate and Magnesium Sulfate Oral Solution is a prescription medicine used by adults to clean the colon before a colonoscopy. Sodium Sulfate, Potassium Sulfate and Magnesium Sulfate Oral Solution cleans your colon by causing you to have diarrhea. Cleaning your colon helps your healthcare provider see the inside of your colon more clearly during your colonoscopy.

It is not known if Sodium Sulfate, Potassium Sulfate and Magnesium Sulfate Oral

Solution is safe and effective in children

Who should not take Sodium Sulfate, Potassium Sulfate and Magnesium Sulfate Oral Solution?

- Do not take Sodium Sulfate, Potassium Sulfate and Magnesium Sulfate Oral Solution if your healthcare provider has told you that you have:
- a blockage in your bowel (obstruction)
- an opening in the wall of your stomach or intestine (bowel perforation)
- problems with food and fluid emptying from your stomach (gastric retention)
- a very dilated intestine (bowel)
- an allergy to any of the ingredients in Sodium Sulfate, Potassium Sulfate and Magnesium Sulfate Oral Solution. See the end of this leaflet for a complete list of ingredients in Sodium Sulfate, Potassium Sulfate and Magnesium Sulfate Oral Solution.

What should I tell my healthcare provider before taking Sodium Sulfate, Potassium Sulfate and Magnesium Sulfate Oral Solution?

Before you take Sodium Sulfate, Potassium Sulfate and Magnesium Sulfate Oral

Solution, tell your healthcare provider if you:

- have heart problems
- have stomach or bowel problems
- have ulcerative colitis
- have problems with swallowing or gastric reflux
- have gout
- have a history of seizures
- are withdrawing from drinking alcohol
- have a low blood salt (sodium) level
- have kidney problems
- any other medical conditions
- are pregnant. It is not known if Sodium Sulfate, Potassium Sulfate and Magnesium Sulfate Oral Solution will harm your unborn baby. Talk to your doctor if you are pregnant or plan to become pregnant.
- are breastfeeding or plan to breastfeed. It is not known if Sodium Sulfate, Potassium Sulfate and Magnesium Sulfate Oral Solution passes into your breast milk. You and your healthcare provider should decide if you will take Sodium Sulfate, Potassium Sulfate and Magnesium Sulfate Oral Solution while breastfeeding.

Tell your healthcare provider about all the medicines you take, including prescription and non-prescription medicines, vitamins, and herbal supplements.

Sodium Sulfate, Potassium Sulfate and Magnesium Sulfate Oral Solution may affect how other medicines work. Medicines taken by mouth may not be absorbed properly when taken within 1 hour before the start of each dose of Sodium Sulfate, Potassium Sulfate and Magnesium Sulfate Oral Solution.

Especially tell your healthcare provider if you take:

- medicines for blood pressure or heart problems
- medicines for kidney problems
- medicines for seizures
- water pills (diuretics)
- non-steroidal anti-inflammatory medicines (NSAID) pain medicines
- laxatives

Ask your healthcare provider or pharmacist for a list of these medicines if you are not sure if you are taking any of the medicines listed above.

Know the medicines you take. Keep a list of them to show your healthcare provider and pharmacist when you get a new medicine.

How should I take Sodium Sulfate, Potassium Sulfate and Magnesium Sulfate Oral Solution?

See the Instructions for Use in the Patient Instructions for Use Booklet for dosing instructions. You must read, understand, and follow these instructions to take Sodium Sulfate, Potassium Sulfate and Magnesium Sulfate Oral Solution the right way.

Take Sodium Sulfate, Potassium Sulfate and Magnesium Sulfate Oral Solution exactly as your healthcare provider tells you to take it.

- Do not drink Sodium Sulfate, Potassium Sulfate and Magnesium Sulfate
- Oral Solution that has not been mixed with water (diluted), it may increase your risk of nausea, vomiting and fluid loss (dehydration).
- Each bottle of Sodium Sulfate, Potassium Sulfate and Magnesium Sulfate Oral Solution must be mixed with water (diluted) before drinking.
- It is important for you to drink the additional prescribed amount of water listed in the Instructions for Use to prevent fluid loss (dehydration).
- Do not take other laxatives while taking sodium sulfate, potassium sulfate and magnesium sulfate oral solution.
- Do not eat solid foods while taking Sodium Sulfate, Potassium Sulfate and Magnesium Sulfate Oral Solution. Only clear liquids are allowed while taking Sodium Sulfate, Potassium Sulfate and Magnesium Sulfate Oral Solution.

What are the possible side effects of Sodium Sulfate, Potassium Sulfate and Magnesium Sulfate Oral Solution?

Sodium Sulfate, Potassium Sulfate and Magnesium Sulfate Oral Solution can cause

serious side effects, including:

- See Section “What is the most important information I should know about Sodium Sulfate, Potassium Sulfate and Magnesium Sulfate Oral Solution?”
- changes in certain blood tests. Your healthcare provider may do blood tests
- after you take Sodium Sulfate, Potassium Sulfate and Magnesium Sulfate Oral
- Solution to check your blood for changes. Tell your healthcare provider if you
- have any symptoms of too much fluid loss, including:
- vomiting
- nausea
- bloating
- dizziness
- stomach (abdominal) cramping
- headache
- urinate less than usual
- trouble drinking clear liquid
- heart problems. Sodium Sulfate, Potassium Sulfate and Magnesium Sulfate Oral Solution may cause irregular heartbeats.
- seizures
- ulcers of the bowel or bowel problems
- worsening gout

The most common side effects of Sodium Sulfate, Potassium Sulfate and Magnesium

Sulfate Oral Solution include:

- discomfort
- bloating
- stomach (abdominal) cramping
- nausea
- vomiting

Tell your healthcare provider if you have any side effect that bothers you or that does not go away.

These are not all the possible side effects of Sodium Sulfate, Potassium Sulfate and Magnesium Sulfate Oral Solution. For more information, ask your healthcare provider or pharmacist.

Call your doctor for medical advice about side effects. You may report side effects to

FDA at 1-800-FDA-1088.

How should I store Sodium Sulfate, Potassium Sulfate and Magnesium Sulfate Oral Solution?

- Store Sodium Sulfate, Potassium Sulfate and Magnesium Sulfate Oral Solution at room temperature, between 59ºF to 86°F (15ºC to 30°C).

Keep Sodium Sulfate, Potassium Sulfate and Magnesium Sulfate Oral Solution and all medicines out of the reach of children.

General information about the safe and effective use of Sodium Sulfate, Potassium Sulfate and Magnesium Sulfate Oral Solution.

Medicines are sometimes prescribed for purposes other than those listed in a Medication Guide. Do not use Sodium Sulfate, Potassium Sulfate and Magnesium Sulfate Oral Solution for a condition for which it was not prescribed. Do not give Sodium Sulfate, Potassium Sulfate and Magnesium Sulfate Oral Solution to other people, even if they are going to have the same procedure you are. It may harm them.

This Medication Guide summarizes important information about Sodium Sulfate, Potassium Sulfate and Magnesium Sulfate Oral Solution. If you would like more information, talk with your healthcare provider. You can ask your pharmacist or healthcare provider for information that is written for healthcare professionals.

For more information, call 1-866-403-7592

What are the ingredients in Sodium Sulfate, Potassium Sulfate and Magnesium Sulfate Oral Solution?

Active ingredients: sodium sulfate, potassium sulfate and magnesium sulfate

Inactive ingredients: sodium benzoate, sucralose, malic acid, citric acid, lemon flavor, purified water

LUPIN and the are registered trademarks of Lupin Pharmaceuticals, Inc.

Lupin Pharmaceuticals, Inc.

Naple, FL 34018

This Medication Guide has been approved by the U.S. Food and Drug Administration.

SAP Code: 276530

Revised 10/2024

PACKAGE LABEL.PRINCIPAL DISPLAY PANEL

Container Label

NDC 43386-700-02

Sodium Sulfate, Potassium Sulfate And Magnesium Sulfate Oral Solution

17.5 g/3.13 g/1.6 g per 6 ounces

Dispense the enclosed Medication Guide to each patient.

This bottle contains 6 ounces (177 mL) of solution

Directions:

Dilute the solution concentrate prior to use. See enclosed booklet for complete dosage and administration instructions. Both 6-ounce bottles are required for a complete prep.

Keep this and other drugs out of reach of children. Store at 25°C (77°F); excursions permitted to 15-30°C (59-86°F).

Carton Label

NDC 43386-700-83

Sodium Sulfate, Potassium Sulfate And Magnesium Sulfate Oral Solution

17.5 g/3.13 g/1.6 g per 6 ounces

This carton contains:

2 6-ounce (177 mL) bottles of solution

(1)19 ounce mixing container with a 16 ounce fill line.

Booklet includes:

1- Medication Guide3

2- Patient Instructions

3- Full Prescribing Information

Dilute the solution concentrate as directed prior to use.

Both 6-ounce bottles are required for a complete prep.

Store at 25°C (77°F): excursions permitted to 15-30°C (59-86°F).

RX only

Panel 1 and 2

Panel 3 and 4